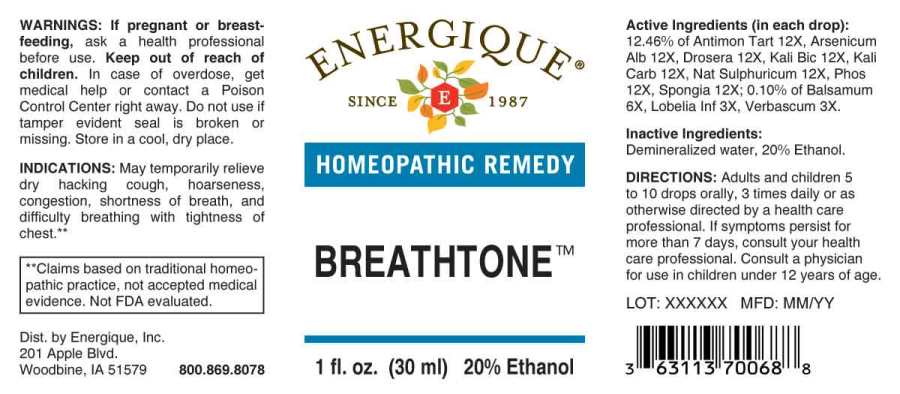 DRUG LABEL: Breathtone
NDC: 44911-0590 | Form: LIQUID
Manufacturer: Energique, Inc.
Category: homeopathic | Type: HUMAN OTC DRUG LABEL
Date: 20230814

ACTIVE INGREDIENTS: LOBELIA INFLATA WHOLE 3 [hp_X]/1 mL; VERBASCUM THAPSUS WHOLE 3 [hp_X]/1 mL; BALSAM PERU 6 [hp_X]/1 mL; ANTIMONY POTASSIUM TARTRATE 12 [hp_X]/1 mL; ARSENIC TRIOXIDE 12 [hp_X]/1 mL; DROSERA ROTUNDIFOLIA WHOLE 12 [hp_X]/1 mL; POTASSIUM DICHROMATE 12 [hp_X]/1 mL; POTASSIUM CARBONATE 12 [hp_X]/1 mL; SODIUM SULFATE 12 [hp_X]/1 mL; PHOSPHORUS 12 [hp_X]/1 mL; SPONGIA OFFICINALIS SKELETON, ROASTED 12 [hp_X]/1 mL
INACTIVE INGREDIENTS: WATER; ALCOHOL

DRUG FACTS:

ACTIVE INGREDIENTS:

(in each drop): 12.46% of Antimonium Tartaricum 12X, Arsenicum Album 12X, Drosera (Rotundifolia) 12X, Kali Bichromicum 12X, Kali Carbonicum 12X, Natrum Sulphuricum 12X, Phosphorous 12X, Spongia Tosta 12X; 0.10% of Balsamum Peruvianum 6X, Lobelia Inflata 3X, Verbascum Thapsus 3X.

INDICATIONS:

May temporarily relieve dry hacking cough, hoarseness, bronchial congestion and hay fever symptoms, and difficulty breathing with tightness of chest from congestion of chest.**

**Claims based on traditional homeopathic practice, not accepted medical evidence. Not FDA evaluated.

WARNINGS:

If pregnant or breast-feeding, ask a health professional before use.

Keep out of reach of children. In case of overdose, get medical help or contact a Poison Control Center right away.

Do not use if tamper evident seal is broken or missing. Store in a cool, dry place.

Keep out of reach of children. In case of overdose, get medical help or contact a Poison Control Center right away.

DIRECTIONS:

Adults and children 5 to 10 drops orally, 3 times daily or as otherwise directed by a health care professional. If symptoms persist for more than 7 days, consult your health care professional. Consult a physician for use in children under 12 years of age.

INDICATIONS:

May temporarily relieve dry hacking cough, hoarseness, bronchial congestion and hay fever symptoms, and difficulty breathing with tightness of chest from congestion of chest.**

**Claims based on traditional homeopathic practice, not accepted medical evidence. Not FDA evaluated.

INACTIVE INGREDIENTS:

Demineralized water, 20% Ethanol.

QUESTIONS:

Dist. by Energique, Inc.

201 Apple Blvd.

Woodbine, IA 51579 800-869-8078

PACKAGE LABEL DISPLAY:

ENERGIQUE

SINCE 1987

HOMEOPATHIC REMEDY

BREATHTONE

1 fl. oz. (30 ml)